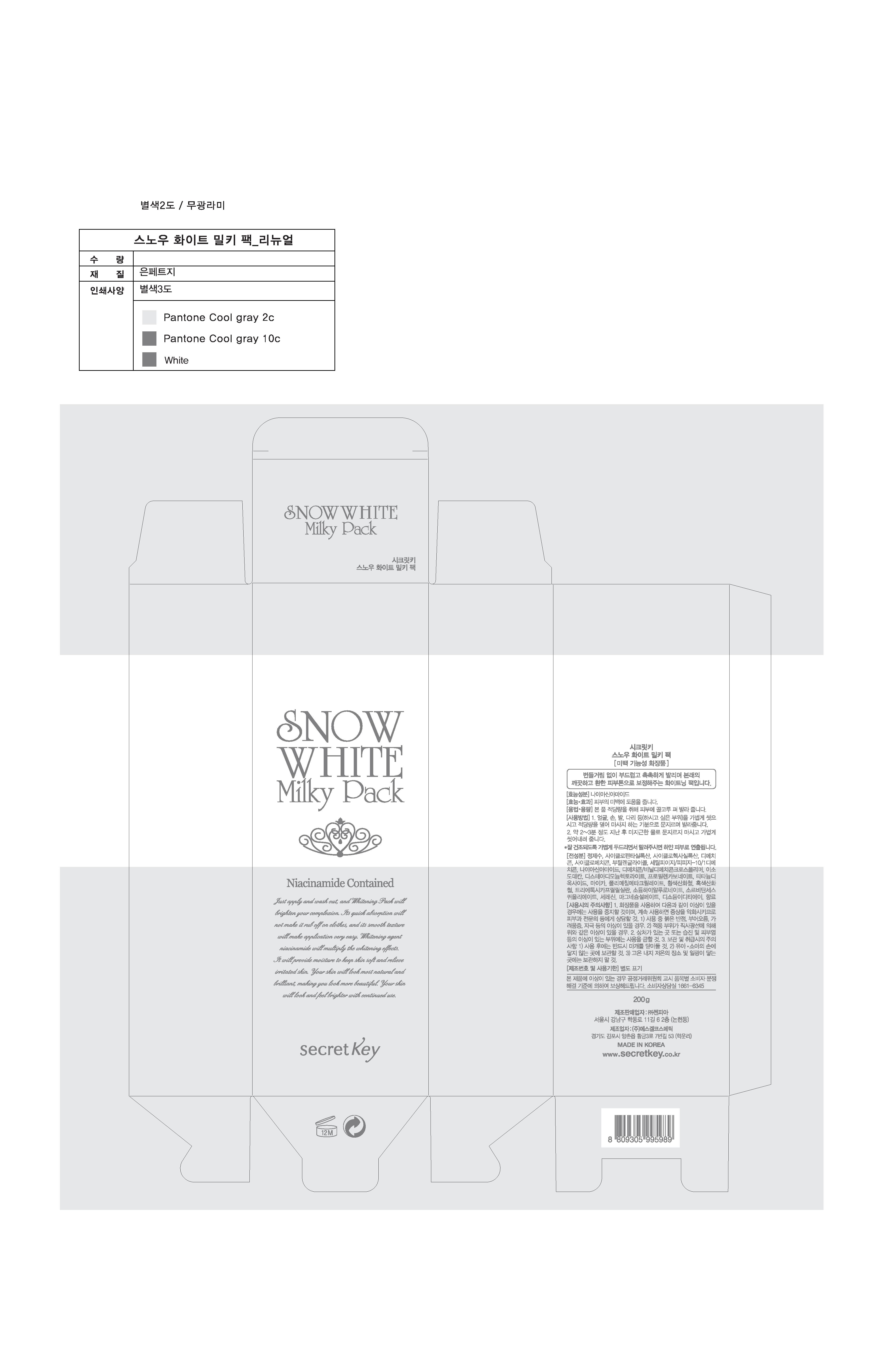 DRUG LABEL: SNOW WHITE MILKY PACK
NDC: 70825-0008 | Form: CREAM
Manufacturer: Zenpia
Category: otc | Type: HUMAN OTC DRUG LABEL
Date: 20181219

ACTIVE INGREDIENTS: NIACINAMIDE 2 g/100 g
INACTIVE INGREDIENTS: WATER; BUTYLENE GLYCOL

Drug Facts

ACTIVE INGREDIENT

niacinamide

INACTIVE INGREDIENT

Water,Cyclopentasiloxan,Cyclohexasiloxan,Dimethicon,Cyclomethicon,Butylene Glycol,Cetyl PEG/PPG-10/1 Dimethicone,Dimethicone/Vinyl Dimethicone Crosspolymer,IsoDodecan,Disteardimonium Hectorite,Propylene Carbonate,Titanium Dioxide,Mica,Polymethyl Methacrylate,CI 77492,CI 77499,Triethoxycaprylylsilane,Sodium Hyaluronate,Sorbitan Sesquioleate,Ceresin,Magnesium Sulfate,Phenoxyethanol,Disodium EDTA,Fragrance

PURPOSE

skin whitening

keep out or reach of the children

INDICATIONS AND USAGE

Apply onto cleaned face or body and gently massage it.

Wash off it with warm water after 2-3 minutes.

WARNINGS

1. Do not use in the following cases(Eczema and scalp wounds)
2.Side Effects
1)Due to the use of this druf if rash, irritation, itching and symptopms of hypersnesitivity occur dicontinue use and consult your phamacisr or doctor
3.General Precautions
1)If in contact with the eyes, wash out thoroughty with water If the symptoms are servere, seek medical advice immediately
2)This product is for exeternal use only. Do not use for internal use
4.Storage and handling precautions
1)If possible, avoid direct sunlight and store in cool and area of low humidity
2)In order to maintain the quality of the product and avoid misuse
3)Avoid placing the product near fire and store out in reach of children

DOSAGE AND ADMINISTRATION

for external use only